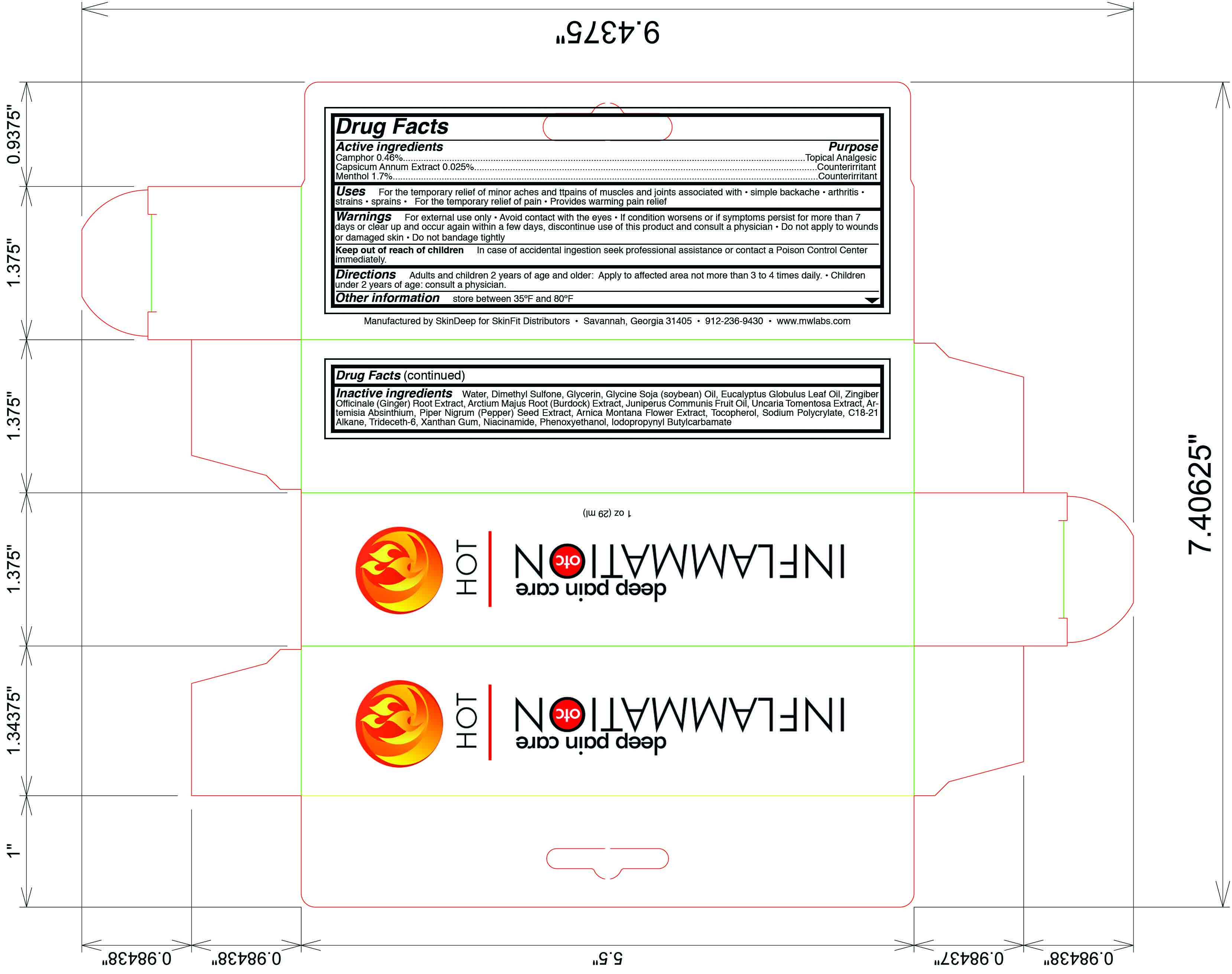 DRUG LABEL: Inflammation OTC
NDC: 45156-5605 | Form: LOTION
Manufacturer: Skin Deep
Category: otc | Type: HUMAN OTC DRUG LABEL
Date: 20110816

ACTIVE INGREDIENTS: Camphor (Natural) 4 g/1000 g; Capsicum 38 g/1000 g; Menthol 17 g/1000 g
INACTIVE INGREDIENTS: Water; Glycerin; Dimethyl Sulfone; Ginger; Soybean Oil; Arctium Lappa Root; Juniper Berry Oil; Cat's Claw; Wormwood; Black Pepper; Arnica Montana Flower; Alpha-Tocopherol; Xanthan Gum; Niacinamide; Phenoxyethanol; Iodopropynyl Butylcarbamate; Corymbia Citriodora Leaf Oil

Drug Fact

Active Ingredient

Camphor (0.46%)

Capsicum Annuum Extract (0.025%)

Menthol (1.7%)

Purpose

Topical Analgesic

Counterirritant

Counterirritant

Uses

For the temporary relief of minor aches and pains of muscles and joints associated with

- simple backache
- arthritis
- strains
- sprains

For the temporary relief of pain
Provides warming pain relief

Warnings

For external use only

Avoid contact with the eyes

Do not apply to wounds or damaged skin

Do not bandage tightly

If condition worsens, or if symptoms persist for more than 7 days or clear up and occur again withing a few days, discontinue use of this product and consult a physician

Keep out of reach of children

In case of accidental ingestion seek professional assistance or contact a poison control center immediately.

Directions

Adults and children 2 years of age and older- Apply to affected area not more than 3 to 4 times daily

Children under 2 years of age- Consult a physician

Inactive Ingredients

water, dimethyl sulfonate, glycerin, glycine soja (soybean) oil, eucalyptus globulus oil, piper nigrum (pepper) seed extract, sodium polycrylate, c18-21 alkane, niacinamide, artemisia absinthium, uncaria tomentosa extract, juniperus communis fruit oil, xanthan gum, zingiber officinate (ginger) root extract, arctium majus root (burdock) extract, arnica montana flower extract, trideceth-6, tocopherol, phenoxyethanol, iodopropynyl butylcarbamate

Questions and Comments

store between 35 F and 80 F

call 1-912-236-9430 weekdays

Principal Display Panel

Inflammation OTC

Deep Pain Care Hot

New wt 1.1 oz. (31 mL)

Manufactured by SkinDeep for SkinFit Distributors

Savannah, GA 31405

Tel: 1-912-236-9430

www.mwlabs.com